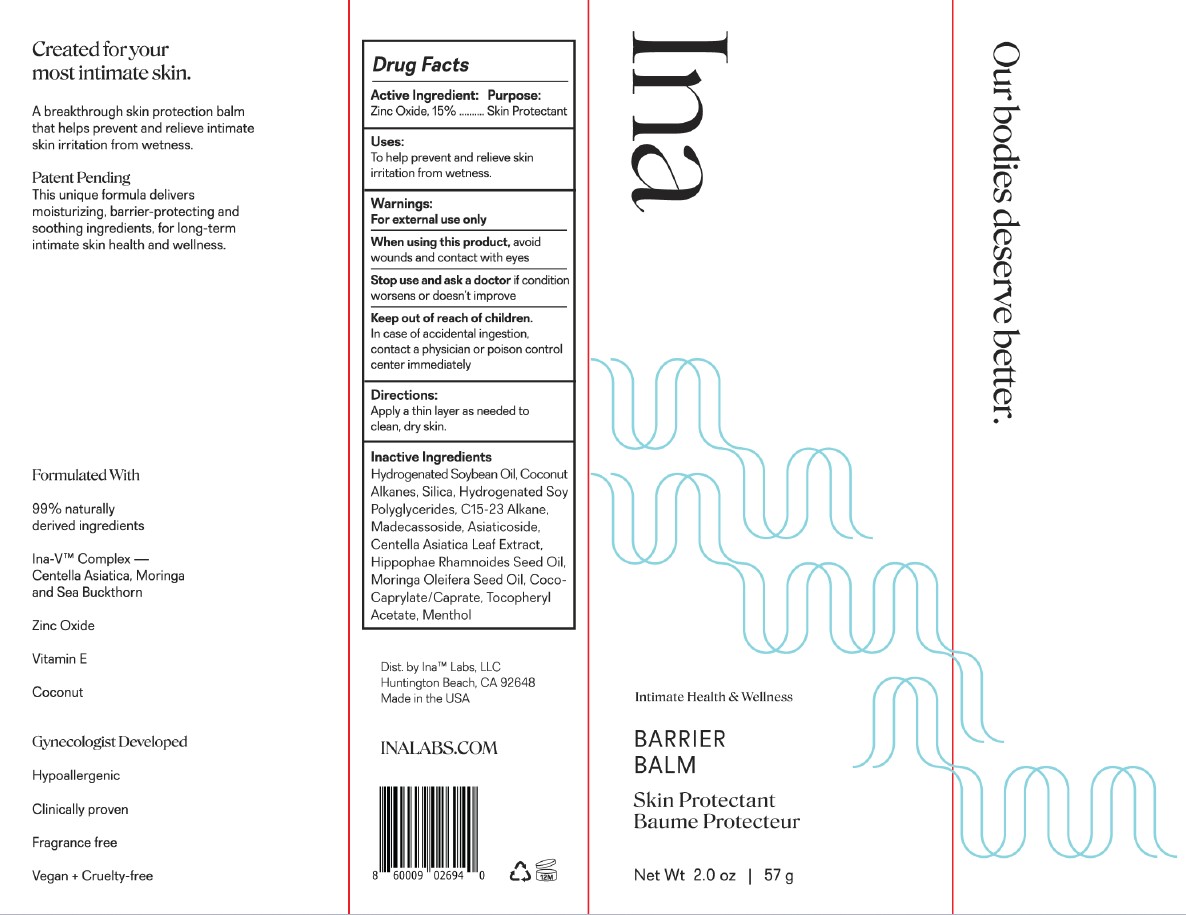 DRUG LABEL: Barrier Balm
NDC: 75523-200 | Form: OINTMENT
Manufacturer: PROJECT CHEMISTRY, INC.
Category: otc | Type: HUMAN OTC DRUG LABEL
Date: 20231028

ACTIVE INGREDIENTS: ZINC OXIDE 15 g/100 g
INACTIVE INGREDIENTS: MORINGA OLEIFERA SEED OIL; CENTELLA ASIATICA LEAF; COCO-CAPRYLATE/CAPRATE; C15-23 ALKANE; ASIATICOSIDE; HIPPOPHAE RHAMNOIDES SEED OIL; MENTHOL; HYDROGENATED SOYBEAN OIL; COCONUT ALKANES; SILICON DIOXIDE; MADECASSOSIDE; .ALPHA.-TOCOPHEROL ACETATE

Ina Labs Barrier Balm

ACTIVE INGREDIENT

Zinc Oxide 15%

PURPOSE

Skin Protectant

Warnings:

For external use only.

When using this product, avoid wounds and contact with eyes.

Stop use and ask a doctor if condition worsens or doesn't improve

Keep out of reach of children. In case of accidental ingestion, contact a physician or poison control center immediately.

Directions:

Apply a thin layer as needed to clean, dry skin.

INACTIVE INGREDIENT

Inactive Ingredients Hydrogenated Soybean Oil, Coconut Alkanes, Silica, Hydrogenated Soy Polyglycerides, C15-23 Alkane, Madecassoside, Asiaticoside, Centella Asiatica Leaf Extract, Hippophae Rhamnoides Seed Oil, Moringa Oleifera Seed Oil, Coco-Caprylate, Tocopheryl Acetate, Menthol.

INDICATIONS AND USAGE

To help prevent and relieve skin irritation from wetness.